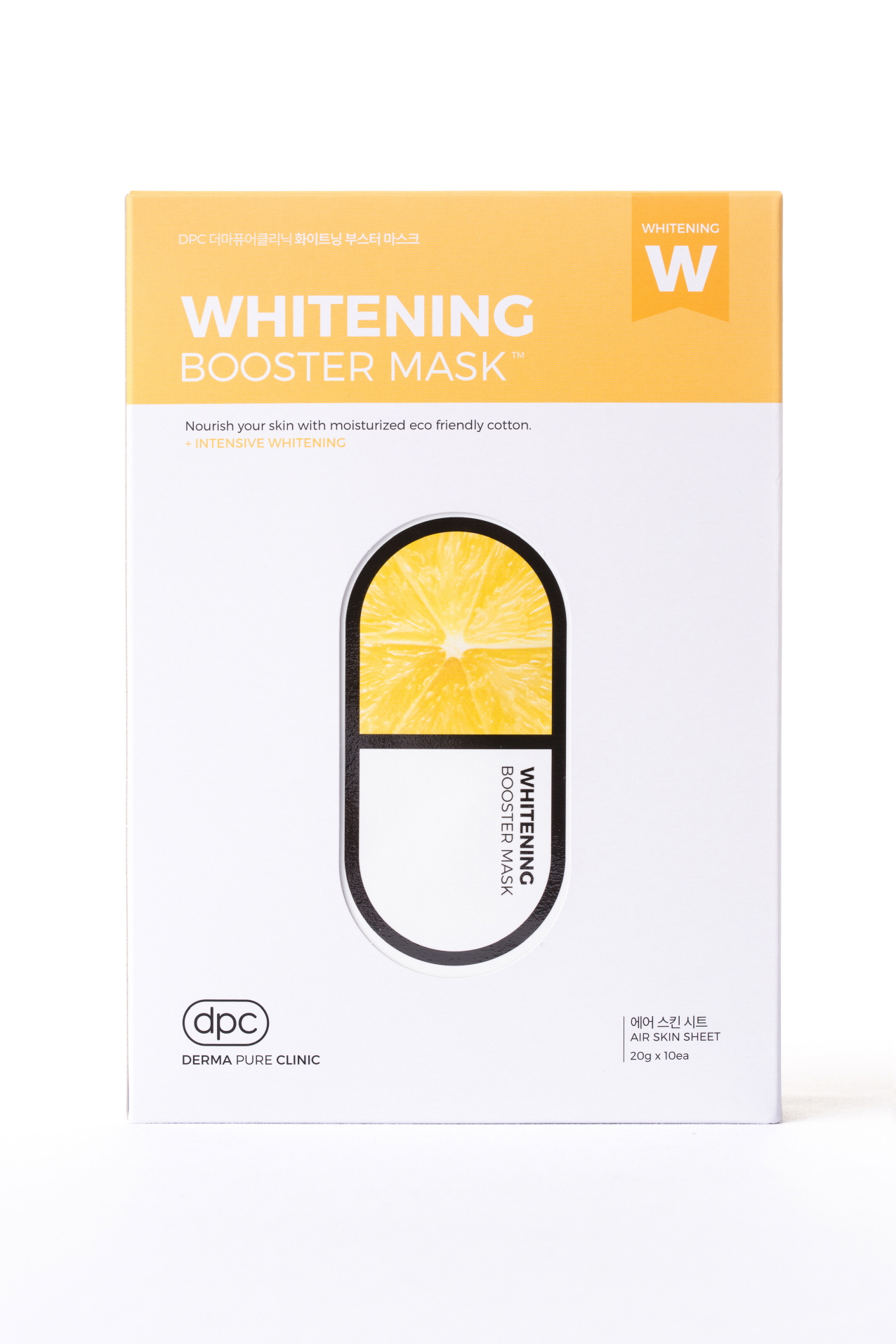 DRUG LABEL: DPC Whitening Booster Mask
NDC: 71673-0003 | Form: LIQUID
Manufacturer: MSCO
Category: otc | Type: HUMAN OTC DRUG LABEL
Date: 20170818

ACTIVE INGREDIENTS: NIACINAMIDE 2 g/100 g
INACTIVE INGREDIENTS: ALLANTOIN; WATER; HYALURONATE SODIUM; GLYCERIN

Drug Facts

ACTIVE INGREDIENT

NIACINAMIDE

INACTIVE INGREDIENT

Water
Dipropylene glycol
Methylpropanediol
Alcohol
Glycerin
Sodium Hyaluronate
1,2-Hexanediol
Biosaccharide Gum-1
Boswellia Serrata Resin Extract
Butylene Glycol
Allantoin
Dipotassium Glycyrrhizate
Beta-Glucan
Hydroxyethylcellulose
Acrylates/c10-30 alkyl acrylate crosspolymer
Simmondsia Chinensis (Jojoba) Seed Oil
Citrus Limon (Lemon) Fruit Extract
Citrus Aurantium Dulcis (Orange) Fruit Water
Oryza Sativa (Rice) Extract
Citrus Aurantifolia (Lime) Fruit Extract
Citrus Paradisi (Grapefruit) Fruit Extract
Caprylic/capric Triglyceride
Hydrogenated Lecithin
Phytosteryl/octyldodecyl Lauroyl Glutamate
Ceramide NP
Polyglyceryl-10 Laurate
Polyglyceryl-10 Myristate
Arginine
Dehydroacetic acid
Chlorphenesin
Disodium EDTA
Glycyrrhiza Glabra (Licorice) Root Extract
Zingiber Officinale (Ginger) Root Extract
Schizandra Chinensis Fruit Extract
Coptis Japonica Root Extract
Camellia Sinensis Leaf Extract
Caprylyl Glycol
Fragrance

PURPOSE

Skin Protectant - Intensive Whitening

keep out of reach of the children

INDICATIONS AND USAGE

1. After cleansing wipe water and apply skin lotion on face.
2. Apply the mask evenly over the face for 10-20 minutes and remove.
3. Pad the left over residue lightly to absorb.

WARNINGS

For external use only.
Avoid contact with eyes. Not for human consumption.
Discontinue use if irritation occurs.
If irritation persists, consult a physician.

DOSAGE AND ADMINISTRATION

for external use only